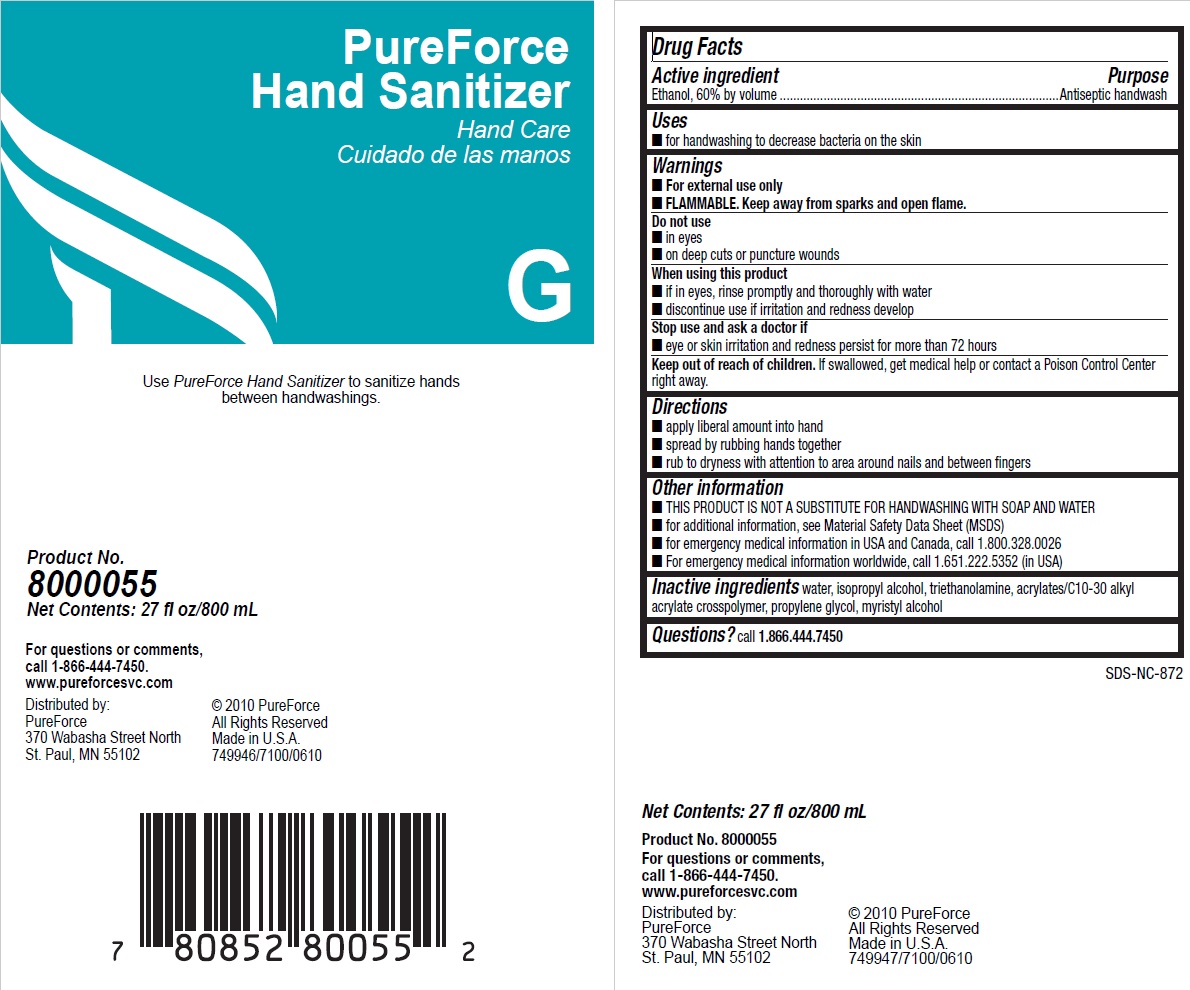 DRUG LABEL: Pureforce
NDC: 47593-473 | Form: SOLUTION
Manufacturer: Ecolab Inc.
Category: otc | Type: HUMAN OTC DRUG LABEL
Date: 20251210

ACTIVE INGREDIENTS: ALCOHOL 60 mL/100 mL
INACTIVE INGREDIENTS: WATER; ISOPROPYL ALCOHOL; TROLAMINE; CARBOMER COPOLYMER TYPE B (ALLYL PENTAERYTHRITOL CROSSLINKED); PROPYLENE GLYCOL; MYRISTYL ALCOHOL

Drug Facts

Active ingredient

Ethanol, 60% by volume

Purpose

Antiseptic handwash

Uses

- for handwashing to decrease bacteria on the skin

Warnings

- For external use only
- FLAMMABLE. Keep away from sparks and open flame.

Do not use

- in eyes
- on deep cuts or puncture wounds

When using this product

- if in eyes, promptly and throughly with water
- discontinue use if irritation and redness develop

Stop use and ask a doctor if

- eye or skin irritation and redness persist for more than 72 hours

Keep out of reach of children. If swallowed, get medical help or contact a Poison Control Center right away.

Directions

- apply liberal amount into hand
- spread by rubbing hands together
- rub to dryness with attention to area around nails and between fingers

INACTIVE INGREDIENT

Inactive ingredients water, isopropyl alcohol, triethanolamine, acrylates/C10-30 alkyl acrylate crosspolymer, propylene glycol, myristyl alcohol

Other information

- THIS PRODUCT IS NOT A SUBSTITUTE FOR HANDWASHING WITH SOAP AND WATER
- for additional information, see Material Safety Data Sheet (MSDS)
- for emergency medical information in USA and Canada, call 1.800.328.0026
- For emergency medical information worldwide, call 1.651.222.5352 (in USA)

Questions? call 1.866.444.7450

Principal display panel and representative label

PureForce

Hand Sanitizer

Hand Care

G

Use Pureforce Hand Sanitizer to sanitize hands

between handwashings.

Product No.

8000055

Net Contents: 27 fl oz/800 mL

For questions or comments,

call 1-866-444-7450

www.pureforcesvc.com

Distribute by:

PureForce

370 Wabasha Street North

St. Paul, MN 55102

copyright 2010 PureForce

All Rights Reserved

Made in U.S.A.

749946/7100/0610